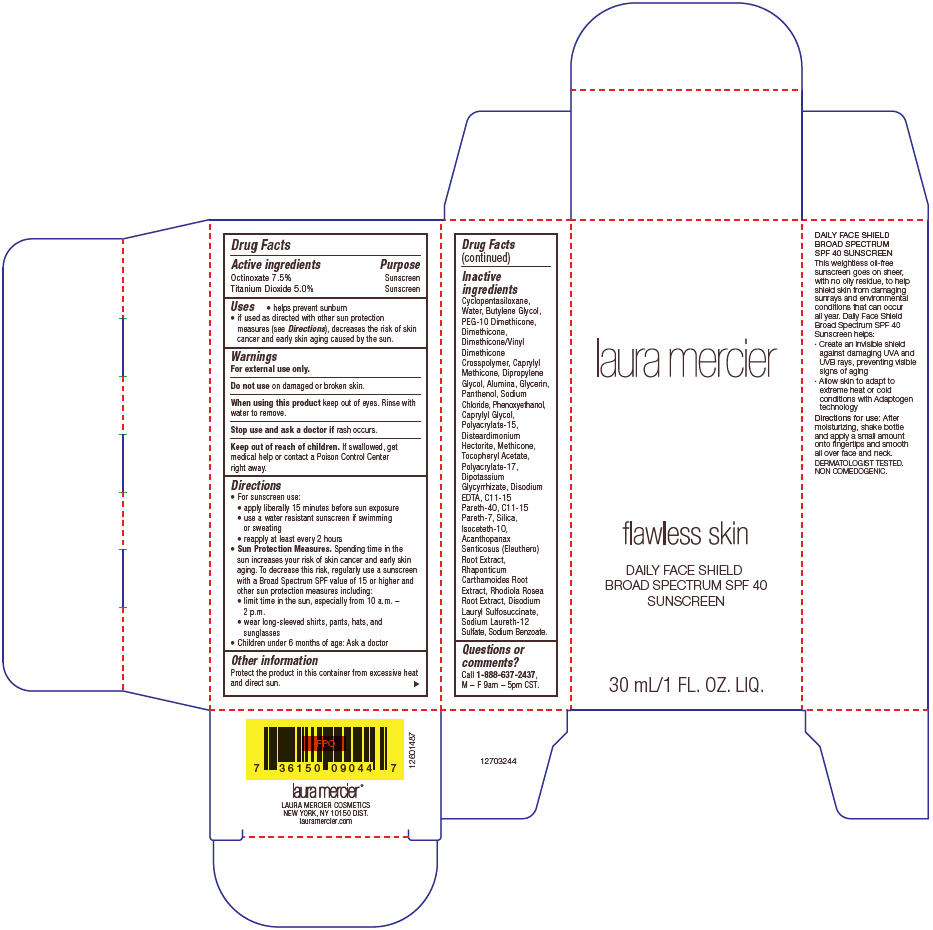 DRUG LABEL: Laura Mercier Flawless Skin Daily Face Shield 
NDC: 58411-413 | Form: CREAM
Manufacturer: Laura Mercier Cosmetics
Category: otc | Type: HUMAN OTC DRUG LABEL
Date: 20180104

ACTIVE INGREDIENTS: OCTINOXATE 75 mg/1 mL; TITANIUM DIOXIDE 50 mg/1 mL
INACTIVE INGREDIENTS: WATER; BUTYLENE GLYCOL; PEG-10 DIMETHICONE (600 CST); DIMETHICONE; CAPRYLYL TRISILOXANE; DIPROPYLENE GLYCOL; ALUMINUM OXIDE; GLYCERIN; PANTHENOL; SODIUM CHLORIDE; PHENOXYETHANOL; CAPRYLYL GLYCOL; DISTEARDIMONIUM HECTORITE; METHICONE (20 CST); .ALPHA.-TOCOPHEROL ACETATE; GLYCYRRHIZINATE DIPOTASSIUM; EDETATE DISODIUM; C11-15 PARETH-40; C11-15 PARETH-7; ISOCETETH-10; ELEUTHERO; RHAPONTICUM CARTHAMOIDES ROOT; SEDUM ROSEUM ROOT; DISODIUM LAURYL SULFOSUCCINATE; SODIUM LAURETH-12 SULFATE; SODIUM BENZOATE

Laura Mercier Flawless Skin Daily Face Shield
SPF 40 Sunscreen

Drug Facts

ACTIVE INGREDIENT

Active ingredients | Purpose
Octinoxate 7.5% | Sunscreen
Titanium Dioxide 5.0% | Sunscreen

Uses

- helps prevent sunburn
- if used as directed with other sun protection measures (see Directions), decreases the risk of skin cancer and early skin aging caused by the sun.

Warnings

For external use only.

Do not use on damaged or broken skin.

When using this product keep out of eyes. Rinse with water to remove.

Stop use and ask a doctor if rash occurs.

Keep out of reach of children. If swallowed, get medical help or contact a Poison Control Center right away.

Directions

- For sunscreen use:
  - apply liberally 15 minutes before sun exposure
  - use a water resistant sunscreen if swimming or sweating
  - reapply at least every 2 hours
- Sun Protection Measures. Spending time in the sun increases your risk of skin cancer and early skin aging. To decrease this risk, regularly use a sunscreen with a Broad Spectrum SPF value of 15 or higher and other sun protection measures including:
  - limit time in the sun, especially from 10 a.m. – 2 p.m.
  - wear long-sleeved shirts, pants, hats, and sunglasses
- Children under 6 months of age: Ask a doctor

Other information

Protect the product in this container from excessive heat and direct sun.

Inactive ingredients

Cyclopentasiloxane, Water, Butylene Glycol, PEG-10 Dimethicone, Dimethicone, Dimethicone/Vinyl Dimethicone Crosspolymer, Caprylyl Methicone, Dipropylene Glycol, Alumina, Glycerin, Panthenol, Sodium Chloride, Phenoxyethanol, Caprylyl Glycol, Polyacrylate-15, Disteardimonium Hectorite, Methicone, Tocopheryl Acetate, Polyacrylate-17, Dipotassium Glycyrrhizate, Disodium EDTA, C11-15 Pareth-40, C11-15 Pareth-7, Silica, Isoceteth-10, Acanthopanax Senticosus (Eleuthero) Root Extract, Rhaponticum Carthamoides Root Extract, Rhodiola Rosea Root Extract, Disodium Lauryl Sulfosuccinate, Sodium Laureth-12 Sulfate, Sodium Benzoate.

Questions or comments?

Call 1-888-637-2437, M – F 9am – 5pm CST .

PRINCIPAL DISPLAY PANEL - 30 mL Tube Carton

laura mercier

flawless skin

DAILY FACE SHIELD
BROAD SPECTRUM SPF 40
SUNSCREEN

30 mL/1 FL. OZ. LIQ.